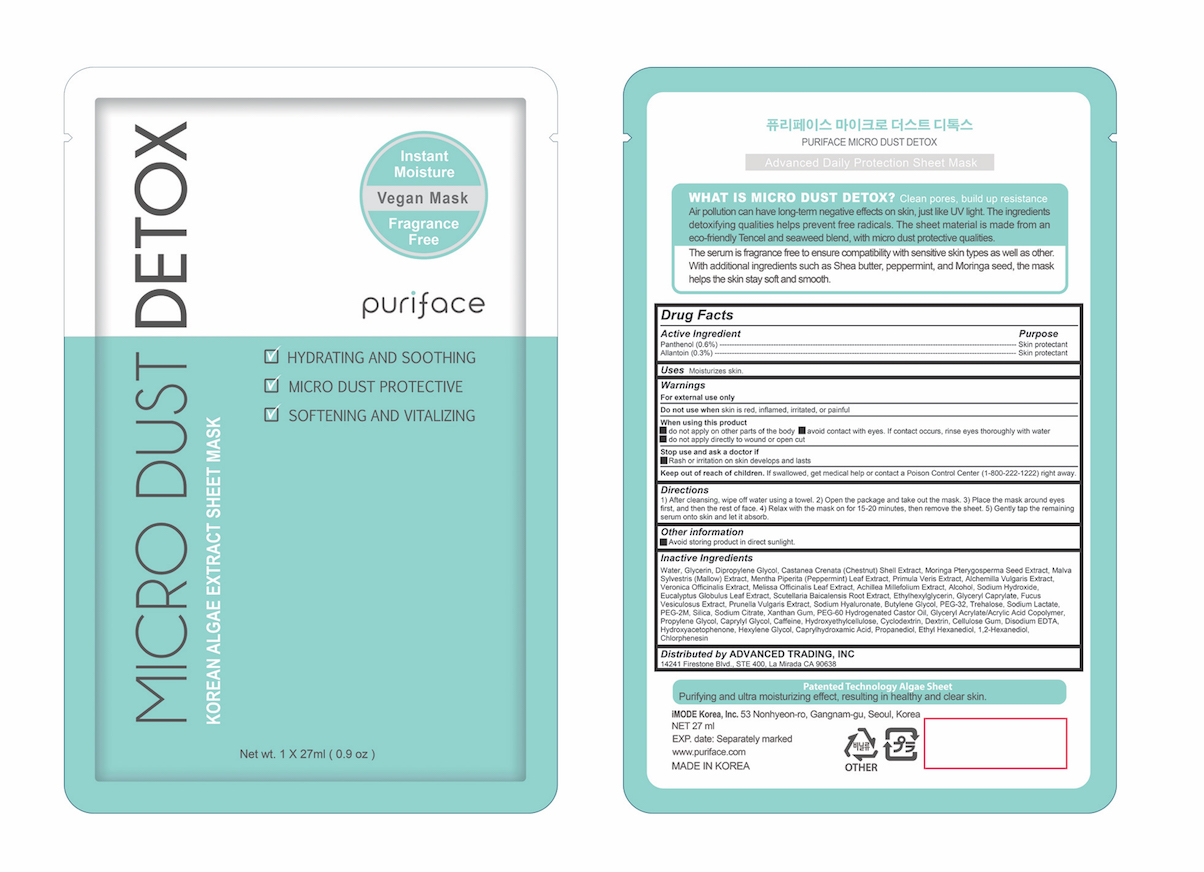 DRUG LABEL: MICRO DUST DETOX
NDC: 71727-101 | Form: PATCH
Manufacturer: iMode Korea, Inc.
Category: otc | Type: HUMAN OTC DRUG LABEL
Date: 20190121

ACTIVE INGREDIENTS: PANTHENOL 0.162 g/27 mL; ALLANTOIN 0.081 g/27 mL
INACTIVE INGREDIENTS: MORINGA OLEIFERA SEED; ALCHEMILLA XANTHOCHLORA FLOWERING TOP; ACHILLEA MILLEFOLIUM; GLYCERIN; PRIMULA VERIS; SODIUM HYDROXIDE; WATER; DIPROPYLENE GLYCOL; CASTANEA CRENATA SHELL; MALVA SYLVESTRIS FLOWERING TOP; MENTHA PIPERITA LEAF; MELISSA OFFICINALIS LEAF; ALCOHOL

MICRO DUST DETOX

Active ingredients

Panthenol (0.6%)

Allantoin (0.3%)

Purpose

Skin protectant

Uses

Moisturizes skin.

Warnings

For external use only

Do not use when skin is red, inflamed, irritated, or painful

When using this product

- do not apply on other parts of the body avoid contact with eyes. If contact occurs, rinse eyes thoroughly with water

- do not apply directly to wound or open cut

Stop use and ask a doctor if

- Rash or irritation on skin develops and lasts

Directions

1) After cleansing, wipe off water using a towel. 2) Open the package and take out the mask. 3) Place the mask around eyes first, and then the rest of face. 4) Relax with the mask on for 15-20 minutes, then remove the sheet. 5) Gently tap the remaining serum onto skin and let it absorb.

Keep out of reach of children

If swallowed, get medical help or contact a Poison Control Center (1-800-222-1222) right away.

Inactive ingredients

Water, Glycerin, Dipropylene Glycol, Castanea Crenata (Chestnut) Shell Extract, Moringa Pterygosperma Seed Extract, Malva Sylvestris (Mallow) Extract, Mentha Piperita (Peppermint) Leaf Extract, Primula Veris Extract, Alchemilla Vulgaris Extract, Veronica Officinalis Extract, Melissa Officinalis Leaf Extract, Achillea Millefolium Extract, Alcohol, Sodium Hydroxide, Eucalyptus Globulus Leaf Extract, Scutellaria Baicalensis Root Extract, Ethylhexylglycerin, Glyceryl Caprylate, Fucus Vesiculosus Extract, Prunella Vulgaris Extract, Sodium Hyaluronate, Butylene Glycol, PEG-32, Trehalose, Sodium Lactate, PEG-2M, Silica, Sodium Citrate, Xanthan Gum, PEG-60 Hydrogenated Castor Oil, Glyceryl Acrylate/Acrylic Acid Copolymer, Propylene Glycol, Caprylyl Glycol, Caffeine, Hydroxyethylcellulose, Cyclodextrin, Dextrin, Cellulose Gum, Disodium EDTA, Hydroxyacetophenone, Hexylene Glycol, Caprylhydroxamic Acid, Propanediol, Ethyl Hexanediol, 1,2-Hexanediol, Chlorphenesin